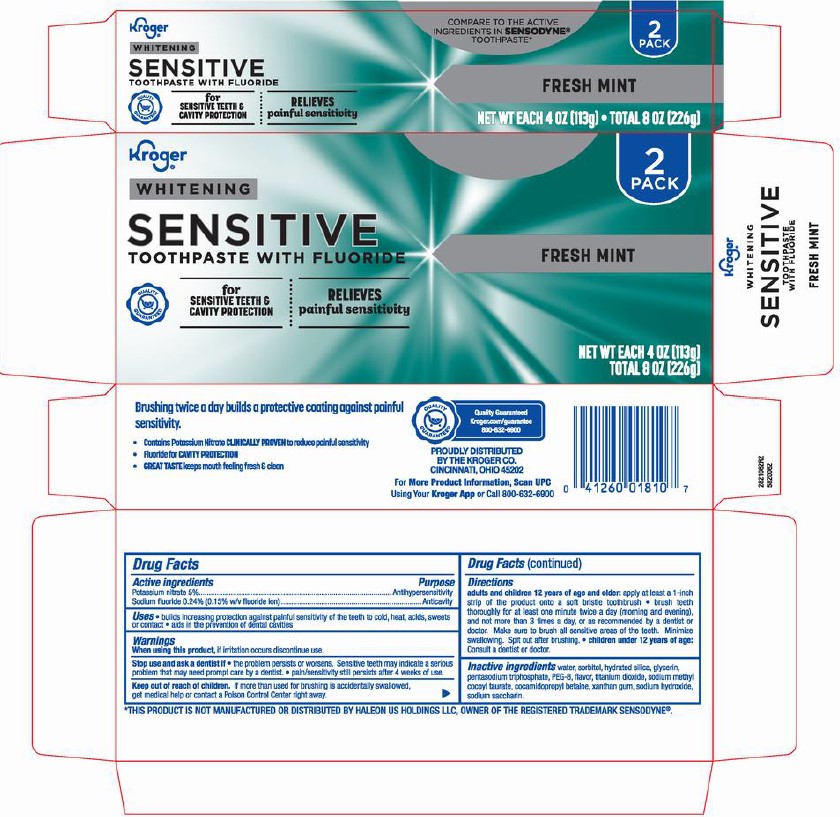 DRUG LABEL: Kroger
NDC: 30142-149 | Form: PASTE, DENTIFRICE
Manufacturer: Kroger
Category: otc | Type: HUMAN OTC DRUG LABEL
Date: 20251215

ACTIVE INGREDIENTS: SODIUM FLUORIDE 0.15 g/100 g; POTASSIUM NITRATE 5 g/100 g
INACTIVE INGREDIENTS: WATER; SACCHARIN SODIUM; SODIUM TRIPOLYPHOSPHATE; POLYETHYLENE GLYCOL 400; SORBITOL; TITANIUM DIOXIDE; SODIUM HYDROXIDE; GLYCERIN; XANTHAN GUM; HYDRATED SILICA; COCAMIDOPROPYL BETAINE; SODIUM METHYL COCOYL TAURATE

5820149, 5820062 Kroger Sens Ex Whitening

Active ingredients / Purpose

Potassium nitrate 5%....................................................Antihypersensitivity

Sodium fluoride 0.24% (0.15% w/v fluoride ion)............Anticavity

Uses

- builds increasing protection against painful sensitivity of the teeth to cold, heat, acids, sweets or contact
- aids in the prevention of dental cavities

When using this product, if irritation occurs discontinue use.

Stop use and ask a dentist if

- the problem persists or worsens. Sensitive teeth may indicate a serious problem that may need prompt care by a dentist
- pain/sensitivity still persists 4 weeks of use.

Keep out of reach of children. If more than used for brushing is accidentally swallowed, get medical help or contact a Poison Control Center right away.

Directions

Brush teeth thoroughly for at least one minute twice a day (morning and evening), and not more than 3 times a day, or as recommended by a dentist or doctor. Make sure to brush all sensitive areas of the teeth. Minimize swallowing. Spit out after brushing.

DOSAGE AND ADMINISTRATION

adults and children under 12 years of age and older: Apply at least a 1-inch strip of the product onto a soft bristle toothbrush. Children under 12 years of age: consult a dentist or a doctor.

Other Information

Store in a cool dry place. Keep tube capped when not in use.

Inactive ingredients

water, sorbitol, hydrated silica, glycerin, pentasodium triphosphate, PEG-8, flavor, titanium dioxide, sodium methyl cocoyl taurate, cocamidopropyl betaine, xanthan gum, sodium hydroxide, sodium saccharin

Keep out of reach of children. If more than used for brushing is accidentally swallowed, get medical help or contact a Poison Control Center right away.